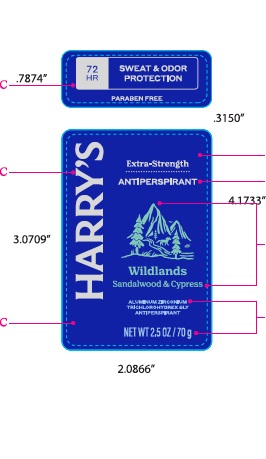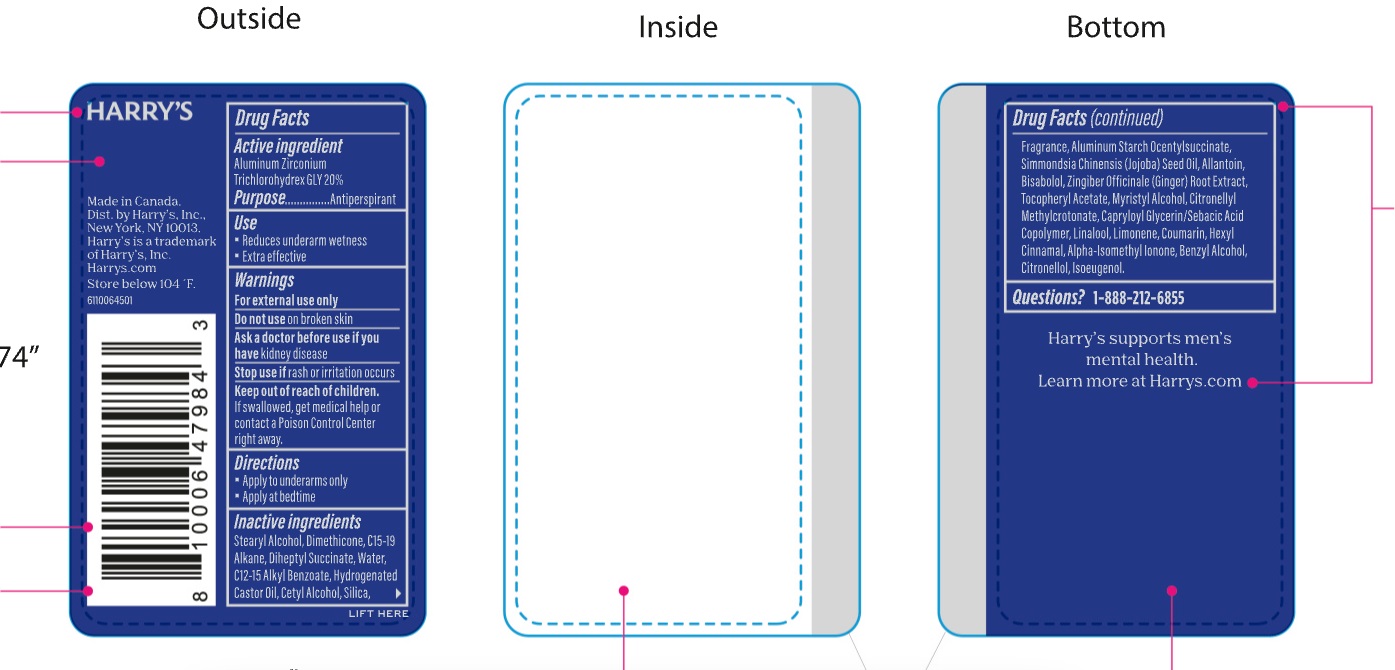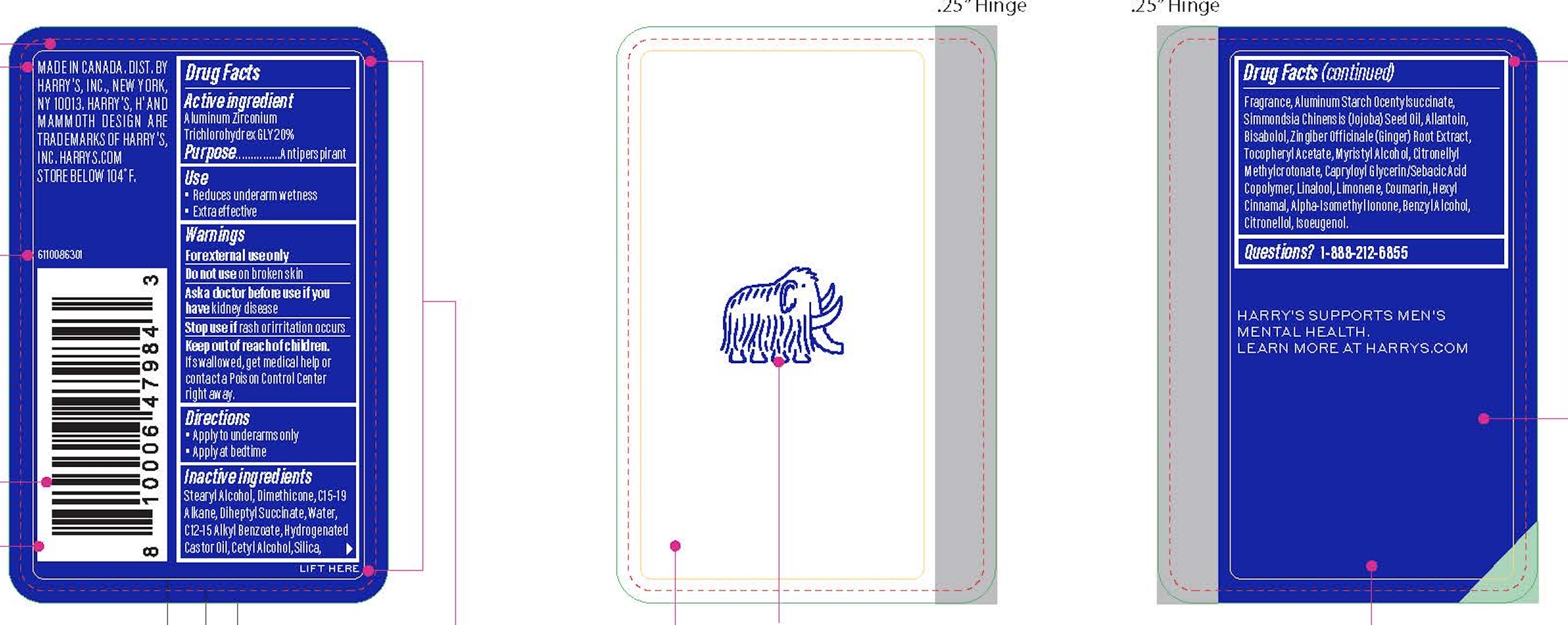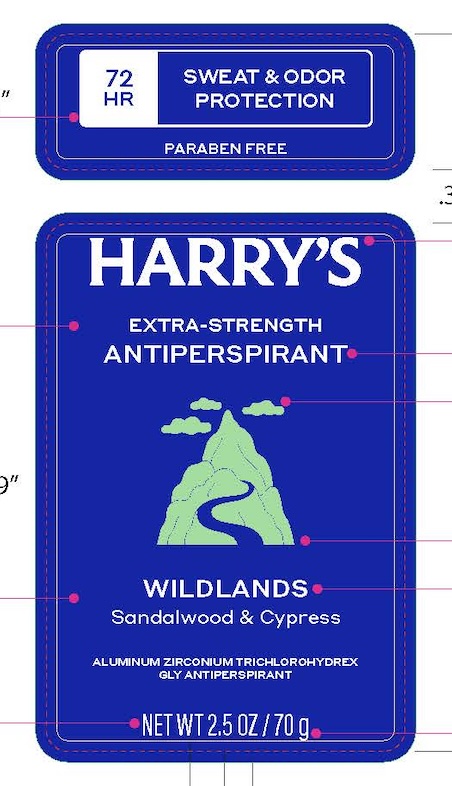 DRUG LABEL: Harrys Extra Strength Antiperspirant Wildlands
NDC: 70533-015 | Form: STICK
Manufacturer: Harry's, Inc.
Category: otc | Type: HUMAN OTC DRUG LABEL
Date: 20251208

ACTIVE INGREDIENTS: ALUMINUM ZIRCONIUM TRICHLOROHYDREX GLY 200 mg/100 g
INACTIVE INGREDIENTS: STEARYL ALCOHOL; DIMETHICONE; CITRONELLYL METHYLCROTONATE; CAPRYLOYL GLYCERIN/SEBACIC ACID COPOLYMER (2000 MPA.S); LIMONENE, (+/-)-; COUMARIN; .ALPHA.-HEXYLCINNAMALDEHYDE; BENZYL ALCOHOL; ISOMETHYL-.ALPHA.-IONONE; .ALPHA.-BISABOLOL, (+/-)-; .BETA.-CITRONELLOL, (R)-; ISOEUGENOL; CETYL ALCOHOL; SILICON DIOXIDE; FRAGRANCE 13576; ALUMINUM STARCH OCTENYLSUCCINATE; WATER; DIHEPTYL SUCCINATE; C15-19 ALKANE; ALKYL (C12-15) BENZOATE; HYDROGENATED CASTOR OIL; JOJOBA OIL; ALLANTOIN; GINGER; .ALPHA.-TOCOPHEROL ACETATE; MYRISTYL ALCOHOL; LINALOOL, (+/-)-

Harrys Extra Strength Antiperspirant Wildlands

Active Ingredient

ALUMINUM ZIRCONIUM TRICHLOROHYDREX GLY 20%

Purpose

Antiperspirant

Use

Reduces underarm wetness.
Extra effective

Warnings

For external use only

Do not use on broken skin

Ask a doctor before use if you have kidney disease

Stop use if rash or irritation occurs

Keep out of reach of children. If swallowed, get medical help or contact a Poison Control Center right away.

Directions

Apply to underarms only. Apply at bedtime

INACTIVE INGREDIENT

STEARYL ALCOHOL, DIMETHICONE, C15-19 ALKANE, DIHEPTYL SUCCINATE, WATER, C12-15 ALKYL BENZOATE, HYDROGENATED CASTOR OIL, CETYL ALCOHOL, SILICA, FRAGRANCE, ALUMINUM STARCH OCENTYLSUCCINATE, SIMMONDSIA CHINENSIS (JOJOBA) SEED OIL, ALLANTOIN, BISABOLOL, ZINGIBER OFFINCALE (GINGER) ROOT EXTRACT, TOCOPHERYL ACETATE, MYRISTYL ALCOHOL, CITRONELLYL METHYLCROTONATE, CAPRYLOYL GLYCERIN/SEBACIC ACID COPOLYMER, LINALOOL, LIMONENE, COUMARIN, HEXYL CINNAMAL, ALPHA-ISOMETHYL IONONE, BENZYL ALCOHOL, CITRONELLOL, ISOEUGENOL.

Questions?

1-888-212-6855